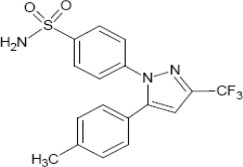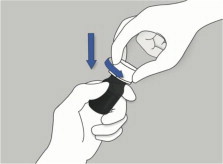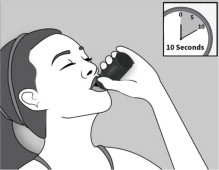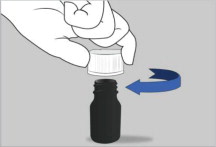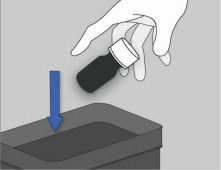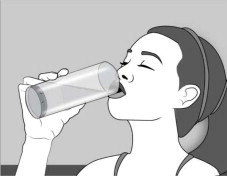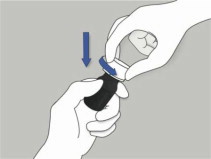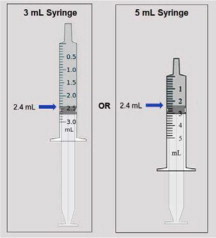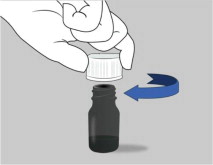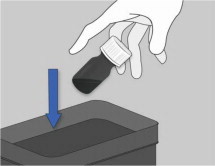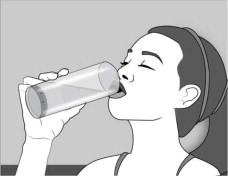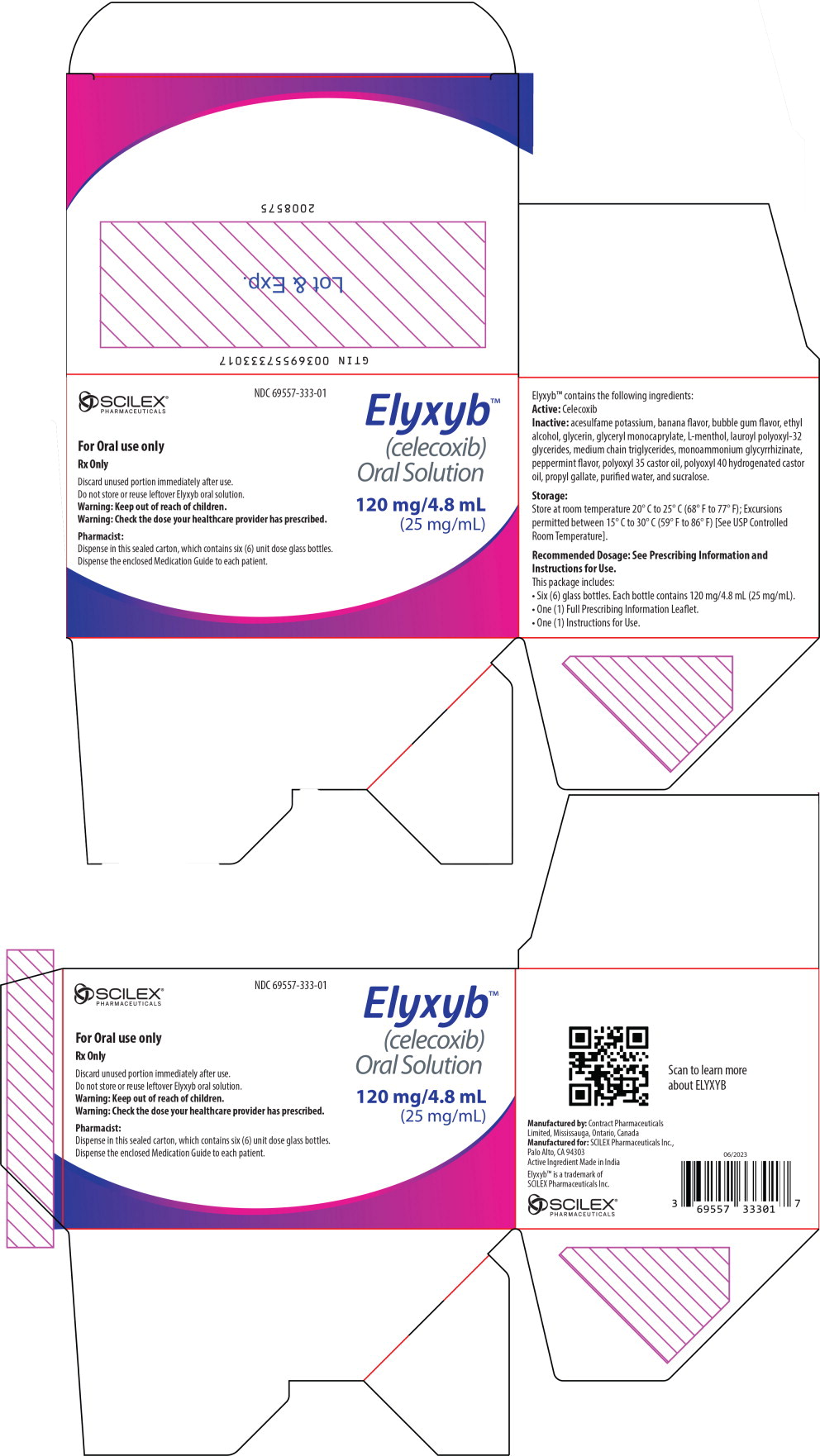 DRUG LABEL: ELYXYB - celecoxib
NDC: 69557-333 | Form: LIQUID
Manufacturer: SCILEX PHARMACEUTICALS INC.
Category: prescription | Type: HUMAN PRESCRIPTION DRUG LABEL
Date: 20241126

ACTIVE INGREDIENTS: CELECOXIB 120 mg/4.8 mL
INACTIVE INGREDIENTS: LAUROYL PEG-32 GLYCERIDES; GLYCERYL MONOCAPRYLATE; MEDIUM-CHAIN TRIGLYCERIDES; POLYOXYL 35 CASTOR OIL; POLYOXYL 40 HYDROGENATED CASTOR OIL; PROPYL GALLATE; LEVOMENTHOL; AMMONIUM GLYCYRRHIZATE; SUCRALOSE; ACESULFAME POTASSIUM; GLYCERIN; ALCOHOL; PEPPERMINT; BANANA

HIGHLIGHTS OF PRESCRIBING INFORMATION

These highlights do not include all the information needed to use ELYXYB safely and effectively. See full prescribing information for ELYXYB.
ELYXYB (celecoxib) oral solution
Initial U.S. Approval: 1998

RECENT MAJOR CHANGES

Warnings and Precautions (5.9) | 11/2024

WARNING: RISK OF SERIOUS CARDIOVASCULAR AND GASTROINTESTINAL EVENTS

See full prescribing information for complete boxed warning.

- Nonsteroidal anti-inflammatory drugs (NSAIDs) cause an increased risk of serious cardiovascular thrombotic events, including myocardial infarction and stroke, which can be fatal. This risk may occur early in the treatment and may increase with duration of use. (5.1)
- ELYXYB is contraindicated in the setting of coronary artery bypass graft (CABG) surgery. (4, 5.1)
- NSAIDs cause an increased risk of serious gastrointestinal (GI) adverse events including bleeding, ulceration, and perforation of the stomach or intestines, which can be fatal. These events can occur at any time during use and without warning symptoms. Elderly patients and patients with a prior history of peptic ulcer disease and/or GI bleeding are at greater risk for serious GI events. (5.2)

1 INDICATIONS AND USAGE

ELYXYB is a nonsteroidal anti-inflammatory drug indicated for the acute treatment of migraine with or without aura in adults (1)

Limitations of Use

ELYXYB is not indicated for the preventive treatment of migraine. (1)

2 DOSAGE AND ADMINISTRATION

- The recommended dose of ELYXYB is 120 mg taken orally, with or without food (2.1)
- The maximum dosage in a 24-hour period is 120 mg (2.1)
- Use ELYXYB for the fewest number of days per month, as needed (2.1)
- Hepatic Impairment: The recommended and maximum dose is 60 mg (2.4 mL) in patients with moderate hepatic impairment (Child-Pugh Class B) (2.2, 8.6, 12.3)
- Poor Metabolizers of CYP2C9 Substrates: The recommended and maximum dose is 60 mg (2.4 mL) in patients who are known or suspected to be CYP2C9 poor metabolizers (2.3, 8.8, 12.5)

3 DOSAGE FORMS AND STRENGTHS

Oral solution, 120 mg/4.8 mL (25 mg/mL) (3)

4 CONTRAINDICATIONS

- Known hypersensitivity to celecoxib, any components of the drug product, or sulfonamides (4)
- History of asthma, urticaria, or other allergic-type reactions after taking aspirin or other NSAIDs (4)
- In the setting of CABG surgery (4)

5 WARNINGS AND PRECAUTIONS

- Hepatotoxicity: Inform patients of warning signs and symptoms of hepatotoxicity. Discontinue if abnormal liver tests persist or worsen or if clinical signs and symptoms of liver disease develop (5.3)
- Hypertension: Patients taking some antihypertensive medications may have impaired response to these therapies when taking NSAIDs. Monitor blood pressure (5.4, 7)
- Heart Failure and Edema: Avoid use of ELYXYB in patients with severe heart failure unless benefits are expected to outweigh risk of worsening heart failure (5.5)
- Renal Toxicity: Monitor renal function in patients with renal or hepatic impairment, heart failure, dehydration, or hypovolemia. Avoid use of ELYXYB in patients with severe renal impairment unless benefits are expected to outweigh risk of worsening renal function (5.6)
- Anaphylactic Reactions: Seek emergency help if an anaphylactic reaction occurs (5.7)
- Exacerbation of Asthma Related to Aspirin Sensitivity: ELYXYB is contraindicated in patients with aspirin-sensitive asthma. Monitor patients with preexisting asthma (without aspirin sensitivity) (5.8)
- Serious Skin Reactions: Discontinue ELYXYB at first appearance of skin rash or other signs of hypersensitivity (5.9)
- Drug Reaction with Eosinophilia and Systemic Symptoms (DRESS): Discontinue and evaluate clinically (5.10)
- Medication Overuse Headache: Detoxification may be necessary (5.11)
- Fetal Toxicity: Limit use of NSAIDs, including ELYXYB, between about 20 to 30 weeks in pregnancy due to the risk of oligohydramnios/fetal renal dysfunction. Avoid use of NSAIDs in women at about 30 weeks gestation and later in pregnancy due to the risks of oligohydramnios/fetal renal dysfunction and premature closure of the fetal ductus arteriosus (5.12, 8.1)
- Hematologic Toxicity: Monitor hemoglobin or hematocrit in patients with any signs or symptoms of anemia (5.13, 7)

6 ADVERSE REACTIONS

- Most common adverse reaction (at least 3% and greater than placebo) is dysgeusia (6.1)
- To report SUSPECTED ADVERSE REACTIONS, contact SCILEX Pharmaceuticals Inc. at 1-866-SCILEX3 or FDA at 1-800-FDA-1088 or www.fda.gov/medwatch

7 DRUG INTERACTIONS

- Drugs that Interfere with Hemostasis (e.g., warfarin, aspirin, SSRIs/SNRIs): Monitor patients for bleeding who are concomitantly taking ELYXYB with drugs that interfere with hemostasis. Concomitant use of ELYXYB and analgesic doses of aspirin is not generally recommended (7)
- ACE Inhibitors, Angiotensin Receptor Blockers (ARB), or Beta- Blockers: Concomitant use with ELYXYB may diminish the antihypertensive effect of these drugs. Monitor blood pressure (7)
- ACE Inhibitors and ARBs: Concomitant use with ELYXYB in elderly, volume depleted, or those with renal impairment may result in deterioration of renal function. In such high-risk patients, monitor for signs of worsening renal function (7)
- Diuretics: NSAIDs can reduce natriuretic effect of furosemide and thiazide diuretics. Monitor patients to assure diuretic efficacy including antihypertensive effects (7)
- Digoxin: Concomitant use with ELYXYB can increase serum concentration and prolong half-life of digoxin. Monitor serum digoxin levels (7)

8 USE IN SPECIFIC POPULATIONS

- Infertility: NSAIDs are associated with reversible infertility. Consider withdrawal of ELYXYB in women who have difficulties conceiving (8.3)

FULL PRESCRIBING INFORMATION

WARNING: RISK OF SERIOUS CARDIOVASCULAR AND GASTROINTESTINAL EVENTS

Cardiovascular Thrombotic Events

- Nonsteroidal anti-inflammatory drugs (NSAIDs) cause an increased risk of serious cardiovascular thrombotic events, including myocardial infarction and stroke, which can be fatal. This risk may occur early in the treatment and may increase with duration of use [see Warnings and Precautions (5.1)].
- ELYXYB is contraindicated in the setting of coronary artery bypass graft (CABG) surgery [see Contraindications (4) and Warnings and Precautions (5.1)].

Gastrointestinal Bleeding, Ulceration, and Perforation

- NSAIDs cause an increased risk of serious gastrointestinal (GI) adverse events including bleeding, ulceration, and perforation of the stomach or intestines, which can be fatal. These events can occur at any time during use and without warning symptoms. Elderly patients and patients with a prior history of peptic ulcer disease and/or GI bleeding are at greater risk for serious (GI) events [see Warnings and Precautions (5.2)].

1 INDICATIONS AND USAGE

ELYXYB is indicated for the acute treatment of migraine with or without aura in adults.

Limitations of Use

ELYXYB is not indicated for the preventive treatment of migraine.

2 DOSAGE AND ADMINISTRATION

2.1 Recommended Dosage

The recommended dose of ELYXYB is 120 mg taken orally, with or without food [see Clinical Pharmacology(12.3) ].

The maximum dosage in a 24-hour period is 120 mg. The safety and effectiveness of a second dose in a 24-hour period have not been established.

Use ELYXYB for the fewest number of days per month, as needed.

2.2 Dosage Modification in Patients with Hepatic Impairment

The recommended and maximum dose in patients with moderate hepatic impairment (Child- Pugh Class B) is 60 mg (2.4 mL) [see Use in Specific Populations (8.6) and Clinical Pharmacology (12.3)]. A calibrated measuring device is recommended to measure and deliver the prescribed dose accurately. A household teaspoon or tablespoon is not an adequate measuring device. Use of ELYXYB in patients with severe hepatic impairment is not recommended.

2.3 Dosage Modification in CYP2C9 Poor Metabolizers

The recommended and maximum dose in patients who are known or suspected to be CYP2C9 poor metabolizers is 60 mg (2.4 mL) [see Use in Specific Populations (8.8) and Clinical Pharmacology (12.5)]. A calibrated measuring device is recommended to measure and deliver the prescribed dose accurately. A household teaspoon or tablespoon is not an adequate measuring device.

3 DOSAGE FORMS AND STRENGTHS

Dosage form: Clear colorless oral solution Strength: 120 mg/4.8 mL (25 mg/mL)

4 CONTRAINDICATIONS

ELYXYB is contraindicated in the following patients:

- Known hypersensitivity (e.g., anaphylactic reactions and serious skin reactions) to celecoxib, any components of the drug product [see Warnings and Precautions (5.7, 5.9)].
- History of asthma, urticaria, or other allergic-type reactions after taking aspirin or other NSAIDs. Severe, sometimes fatal, anaphylactic reactions to NSAIDs have been reported in such patients [see Warnings and Precautions (5.7, 5.8)].
- In the setting of coronary artery bypass graft (CABG) surgery [see Warnings and Precautions (5.1)].
- In patients who have demonstrated allergic-type reactions to sulfonamides [see Warnings and Precautions (5.7)].

5 WARNINGS AND PRECAUTIONS

5.1 Cardiovascular Thrombotic Events

Clinical trials of several cyclooxygenase (COX-2) selective and nonselective NSAIDs of up to three years duration have shown an increased risk of serious cardiovascular (CV) thrombotic events, including myocardial infarction (MI) and stroke, which can be fatal. Based on available data, it is unclear that the risk for CV thrombotic events is similar for all NSAIDs. The relative increase in serious CV thrombotic events over baseline conferred by NSAID use appears to be similar in those with and without known CV disease or risk factors for CV disease. However, patients with known CV disease or risk factors had a higher absolute incidence of excess serious CV thrombotic events, due to their increased baseline rate. Some observational studies found that this increased risk of serious CV thrombotic events began as early as the first weeks of treatment. The increase in CV thrombotic risk has been observed most consistently at higher doses.

In a trial with celecoxib capsules, there was about a threefold increased risk of the composite endpoint of cardiovascular death, MI, or stroke for the celecoxib 400 mg twice daily and celecoxib 200 mg twice daily treatment arms compared to placebo. The increases in both celecoxib dose groups versus placebo-treated patients were mainly due to an increased incidence of myocardial infarction.

To minimize the potential risk for an adverse CV event in NSAID-treated patients, use ELYXYB for the fewest number of days per month as needed, based on individual treatment goals.

Physicians and patients should remain alert for the development of such events, throughout the entire treatment course, even in the absence of previous CV symptoms. Patients should be informed about the symptoms of serious CV events and the steps to take if they occur.

There is no consistent evidence that concurrent use of aspirin mitigates the increased risk of serious CV thrombotic events associated with NSAID use. The concurrent use of aspirin and an NSAID, such as ELYXYB, increases the risk of serious gastrointestinal (GI) events [see Warnings and Precautions (5.2)].

Status Post Coronary Artery Bypass Graft (CABG) Surgery

Two large, controlled clinical trials of a COX-2 selective NSAID administered in the first 10 to 14 days following CABG surgery found an increased incidence of myocardial infarction and stroke. NSAIDs, including ELYXYB, are contraindicated in the setting of CABG [see Contraindications (4)].

Post-MI Patients

Observational studies conducted in the Danish National Registry have demonstrated that patients treated with NSAIDs in the post-MI period were at increased risk of reinfarction, CV-related death, and all-cause mortality beginning in the first week of treatment. In this same cohort, the incidence of death in the first year post-MI was 20 per 100 person years in NSAID-treated patients compared to 12 per 100 person years in non-NSAID exposed patients. Although the absolute rate of death declined somewhat after the first year post-MI, the increased relative risk of death in NSAID users persisted over at least the next four years of follow-up.

Avoid the use of ELYXYB in patients with a recent MI unless the benefits are expected to outweigh the risk of recurrent CV thrombotic events. If ELYXYB is used in patients with a recent MI, monitor patients for signs of cardiac ischemia.

5.2 Gastrointestinal Bleeding, Ulceration and Perforation

NSAIDs, including ELYXYB, can cause serious gastrointestinal (GI) adverse events including inflammation, bleeding, ulceration, and perforation of the esophagus, stomach, small intestine, or large intestine, which can be fatal. These serious adverse events can occur at any time, with or without warning symptoms, in patients treated with celecoxib. Only one in five patients who develop a serious upper GI adverse event on NSAID therapy is symptomatic. Upper GI ulcers, gross bleeding, or perforation caused by NSAIDs occurred in approximately 1% of patients treated for 3 to 6 months, and in about 2% to 4% of patients treated for one year. However, even short-term NSAID therapy is not without risk.

Risk Factors for GI Bleeding, Ulceration, and Perforation

Patients with a prior history of peptic ulcer disease and/or GI bleeding who used NSAIDs had a greater than 10-fold increased risk for developing a GI bleed compared to patients without these risk factors. Other factors that increase the risk of GI bleeding in patients treated with NSAIDs include longer duration of NSAID therapy; concomitant use of oral corticosteroids, antiplatelet drugs (such as aspirin), anticoagulants; or selective serotonin reuptake inhibitors (SSRIs); smoking; use of alcohol; older age; and poor general health status. Most postmarketing reports of fatal GI events occurred in elderly or debilitated patients. Additionally, patients with severe liver impairment and/or coagulopathy are at increased risk for GI bleeding.

Strategies to Minimize the GI Risks in NSAID-treated patients

- Avoid administration of more than one NSAID at a time.
- Avoid use in patients at higher risk unless benefits are expected to outweigh the increased risk of bleeding. For such patients, as well as those with active GI bleeding, consider alternate therapies other than NSAIDs.
- Remain alert for signs and symptoms of GI ulceration and bleeding during NSAID therapy.
- If a serious GI adverse event is suspected, promptly initiate evaluation and treatment, and discontinue ELYXYB until a serious GI adverse event is ruled out.
- In the setting of concomitant use of low-dose aspirin for cardiac prophylaxis, monitor patients more closely for evidence of GI bleeding [see Drug Interactions (7)].

5.3 Hepatotoxicity

Elevations of ALT or AST (three or more times the upper limit of normal [ULN]) have been reported in approximately 1% of NSAID-treated patients in clinical trials. In addition, rare, sometimes fatal, cases of severe hepatic injury, including fulminant hepatitis, liver necrosis, and hepatic failure have been reported.

Elevations of ALT or AST (less than three times ULN) may occur in up to 15% of patients treated with NSAIDs, including ELYXYB.

In controlled clinical trials of celecoxib capsules, the incidence of borderline elevations (greater than or equal to 1.2 times and less than 3 times the upper limit of normal) of liver associated enzymes was 6% for celecoxib and 5% for placebo, and approximately 0.2% of patients taking celecoxib and 0.3% of patients taking placebo had notable elevations of ALT and AST.

If clinical signs and symptoms consistent with liver disease develop, or if systemic manifestations occur (e.g., nausea, fatigue, pruritus, jaundice, right upper quadrant tenderness, and/or flu-like symptoms), discontinue ELYXYB immediately, and perform a clinical evaluation of the patient.

5.4 Hypertension

NSAIDs, including ELYXYB, can lead to new onset of hypertension or worsening of preexisting hypertension, either of which may contribute to the increased incidence of CV events. Use NSAIDs, including ELYXYB, with caution in patients with hypertension. Monitor blood pressure (BP) during the initiation of ELYXYB treatment and throughout the course of therapy.

Patients taking angiotensin converting enzyme (ACE) inhibitors, thiazide diuretics, or loop diuretics may have impaired response to these therapies when taking NSAIDs [see Drug Interactions (7)].

5.5 Heart Failure and Edema

The Coxib and traditional NSAID Trialists' Collaboration meta-analysis of randomized controlled trials demonstrated an approximately two-fold increase in hospitalizations for heart failure in COX-2 selective-treated patients and nonselective NSAID-treated patients compared to placebo-treated patients. In a Danish National Registry study of patients with heart failure, NSAID use increased the risk of MI, hospitalization for heart failure, and death.

Additionally, fluid retention and edema have been observed in some patients treated with NSAIDs. Use of ELYXYB may blunt the CV effects of several therapeutic agents used to treat these medical conditions (e.g., diuretics, ACE inhibitors, or angiotensin receptor blockers [ARBs]) [see Drug Interactions (7)] .

In a clinical study, the cumulative rates at 9 months of peripheral edema in patients on celecoxib capsules 400 mg twice daily, ibuprofen 800 mg three times daily, and diclofenac 75 mg twice daily were 4.5%, 6.9%, and 4.7%, respectively.

Avoid the use of ELYXYB in patients with severe heart failure unless the benefits are expected to outweigh the risk of worsening heart failure. If ELYXYB is used in patients with severe heart failure, monitor patients for signs of worsening heart failure.

5.6 Renal Toxicity and Hyperkalemia

Renal Toxicity

Long-term administration of NSAIDs, including celecoxib, the active ingredient in ELYXYB, has resulted in renal papillary necrosis and other renal injury.

Renal toxicity has also been seen in patients in whom renal prostaglandins have a compensatory role in the maintenance of renal perfusion. In these patients, administration of an NSAID may cause a dose-dependent reduction in prostaglandin formation and, secondarily, in renal blood flow, which may precipitate overt renal decompensation. Patients at greatest risk of this reaction are those with impaired renal function, dehydration, hypovolemia, heart failure, liver dysfunction, those taking diuretics, ACE-inhibitors or the ARBs, and the elderly. Discontinuation of NSAID therapy is usually followed by recovery to the pretreatment state.

No information is available from controlled clinical studies regarding the use of celecoxib in patients with severe renal impairment. The renal effects of celecoxib may hasten the progression of renal dysfunction in patients with preexisting renal disease.

Correct volume status in dehydrated or hypovolemic patients prior to initiating ELYXYB. Monitor renal function in patients with renal or hepatic impairment, heart failure, dehydration, or hypovolemia during use of ELYXYB [see Drug Interactions (7)]. ELYXYB is not recommended in patients with severe renal impairment.

Hyperkalemia

Increases in serum potassium concentration, including hyperkalemia, have been reported with use of NSAIDs, even in some patients without renal impairment. In patients with normal renal function, these effects have been attributed to a hyporeninemic-hypoaldosteronism state.

5.7 Anaphylactic Reactions

Celecoxib has been associated with anaphylactic reactions in patients with and without known hypersensitivity to celecoxib and in patients with aspirin sensitive asthma. Celecoxib is a sulfonamide and both NSAIDs and sulfonamides may cause allergic type reactions including anaphylactic symptoms and life-threatening or less severe asthmatic episodes in certain susceptible people [see Contraindications (4) and Warnings and Precautions (5.8)].

5.8 Exacerbation of Asthma Related to Aspirin Sensitivity

A subpopulation of patients with asthma may have aspirin-sensitive asthma which may include chronic rhinosinusitis complicated by nasal polyps; severe, potentially fatal bronchospasm; and/or intolerance to aspirin and other NSAIDs. Because cross-reactivity between aspirin and other NSAIDs has been reported in such aspirin-sensitive patients, ELYXYB is contraindicated in patients with this form of aspirin sensitivity [see Contraindications (4)]. When ELYXYB is used in patients with preexisting asthma (without known aspirin sensitivity), monitor patients for changes in the signs and symptoms of asthma.

5.9 Serious Skin Reactions

Serious skin reactions have occurred following treatment with celecoxib, including erythema multiforme, exfoliative dermatitis, Stevens-Johnson Syndrome (SJS), toxic epidermal necrolysis (TEN), drug reaction with eosinophilia and systemic symptoms (DRESS) [see Warnings and Precautions (5.10)] , acute generalized exanthematous pustulosis (AGEP), and fixed drug eruption (FDE), which may present as a more severe variant known as generalized bullous fixed drug eruption (GBFDE). These serious events may occur without warning and can be fatal.

Inform patients about the signs and symptoms of serious skin reactions, and to discontinue the use of ELYXYB at the first appearance of skin rash or any other sign of hypersensitivity.

ELYXYB is contraindicated in patients with previous serious skin reactions to NSAIDs [see Contraindications (4)].

5.10 Drug Reaction with Eosinophilia and Systemic Symptoms (DRESS)

Drug Reaction with Eosinophilia and Systemic Symptoms (DRESS) has been reported in patients taking NSAIDs such as ELYXYB. Some of these events have been fatal or life- threatening. DRESS typically, although not exclusively, presents with fever, rash, lymphadenopathy, and/or facial swelling. Other clinical manifestations may include hepatitis, nephritis, hematological abnormalities, myocarditis, or myositis. Sometimes symptoms of DRESS may resemble an acute viral infection. Eosinophilia is often present. Because this disorder is variable in its presentation, other organ systems not noted here may be involved. It is important to note that early manifestations of hypersensitivity, such as fever or lymphadenopathy, may be present even though rash is not evident. If such signs or symptoms are present, discontinue ELYXYB and evaluate the patient immediately.

5.11 Medication Overuse Headache

Overuse of acute migraine drugs (e.g., ergotamine, triptans, opioids, nonsteroidal anti- inflammatory drugs or combination of these drugs for 10 or more days per month), including ELYXYB, may lead to exacerbation of headache (medication overuse headache). Medication overuse headache may present as migraine-like daily headaches or as a marked increase in frequency of migraine attacks. Detoxification of patients, including withdrawal of the overused drugs and treatment of withdrawal symptoms (which often includes a transient worsening of headache) may be necessary.

5.12 Fetal Toxicity

Premature Closure of Fetal Ductus Arteriosus

Avoid use of NSAIDs, including ELYXYB, in pregnant women at about 30 weeks gestation and later. NSAIDs, including ELYXYB, increase the risk of premature closure of the fetal ductus arteriosus at approximately this gestational age.

Oligohydramnios/Neonatal Renal Impairment

Use of NSAIDs, including ELYXYB, at about 20 weeks gestation or later in pregnancy may cause fetal renal dysfunction leading to oligohydramnios and, in some cases, neonatal renal impairment. These adverse outcomes are seen, on average, after days to weeks of treatment, although oligohydramnios has been infrequently reported as soon as 48 hours after NSAID initiation. Oligohydramnios is often, but not always, reversible with treatment discontinuation. Complications of prolonged oligohydramnios may, for example, include limb contractures and delayed lung maturation. In some postmarketing cases of impaired neonatal renal function, invasive procedures such as exchange transfusion or dialysis were required.

If NSAID treatment is necessary between about 20 weeks and 30 weeks gestation, limit ELYXYB use to the lowest effective dose and shortest duration possible. Consider ultrasound monitoring of amniotic fluid if ELYXYB treatment extends beyond 48 hours. Discontinue ELYXYB if oligohydramnios occurs and follow up according to clinical practice [see Use in Specific Populations (8.1)] .

5.13 Hematological Toxicity

Anemia has occurred in NSAID-treated patients. This may be due to occult or gross blood loss, fluid retention, or an incompletely described effect on erythropoiesis. If a patient treated with ELYXYB has any signs or symptoms of anemia, monitor hemoglobin or hematocrit.

In controlled clinical trials of celecoxib capsules, the incidence of anemia was 0.6% with celecoxib and 0.4% with placebo. Patients on long-term treatment with ELYXYB should have their hemoglobin or hematocrit checked if they exhibit any signs or symptoms of anemia or blood loss.

NSAIDs, including ELYXYB, may increase the risk of bleeding events. Co-morbid conditions such as coagulation disorders or concomitant use of warfarin, other anticoagulants, antiplatelet drugs (e.g., aspirin), SSRIs, and serotonin norepinephrine reuptake inhibitors (SNRIs) may increase this risk. Monitor these patients for signs of bleeding [see Drug Interactions (7)].

5.14 Masking of Inflammation and Fever

The pharmacological activity of celecoxib in reducing inflammation, and possibly fever, may diminish the utility of diagnostic signs in detecting infections.

5.15 Laboratory Monitoring

Because serious GI bleeding, hepatotoxicity, and renal injury can occur without warning symptoms or signs, consider monitoring patients on long-term NSAID, including ELYXYB, treatment with a CBC and a chemistry profile periodically [see Warnings and Precautions (5.2, 5.3, 5.6)].

In controlled clinical trials with celecoxib capsules, elevated BUN occurred more frequently in patients receiving celecoxib compared with patients on placebo. This laboratory abnormality was also seen in patients who received comparator NSAIDs in these studies. The clinical significance of this abnormality has not been established.

5.16 Disseminated Intravascular Coagulation (DIC)

ELYXYB is not indicated in pediatric patients or for the treatment of juvenile rheumatoid arthritis (JRA). Disseminated intravascular coagulation has occurred with use of celecoxib capsules in pediatric patients with systemic onset JRA, which required monitoring for signs and symptoms of abnormal clotting or bleeding.

6 ADVERSE REACTIONS

The following adverse reactions are discussed in greater detail in other sections of the labeling:

- Cardiovascular Thrombotic Events [see Warnings and Precautions (5.1)]
- GI Bleeding, Ulceration, and Perforation [see Warnings and Precautions (5.2)]
- Hepatotoxicity [see Warnings and Precautions (5.3)]
- Hypertension [see Warnings and Precautions (5.4)]
- Heart Failure and Edema [see Warnings and Precautions (5.5)]
- Renal Toxicity and Hyperkalemia [see Warnings and Precautions (5.6)]
- Anaphylactic Reactions [see Warnings and Precautions (5.7)]
- Exacerbation of Asthma Related to Aspirin Sensitivity [see Warnings and Precautions (5.8)]
- Serious Skin Reactions [see Warnings and Precautions (5.9)]
- Drug Reaction with Eosinophilia and Systemic Symptoms (DRESS) [see Warnings and Precautions (5.10)]
- Medication Overuse Headache [see Warnings and Precautions (5.11)]
- Fetal Toxicity [see Warnings and Precautions (5.12)]
- Hematologic Toxicity [see Warnings and Precautions (5.13)]

6.1 Clinical Trials Experience

Because clinical trials are conducted under widely varying conditions, adverse reaction rates observed in the clinical trials of a drug cannot be directly compared to the rates in the clinical trials of another drug and may not reflect the rates observed in practice.

The safety of ELYXYB was evaluated in 815 patients who received at least one dose of ELYXYB in two, randomized, double-blind, placebo-controlled trials (Study 1 and 2) in adult patients with migraine [see Clinical Studies (14)].

The most common (at least 2% of patients who received ELYXYB and greater than placebo) adverse reaction in Study 1 and Study 2 was dysgeusia, which occurred in 3% of patients who received ELYXYB compared to 1% of patients who received placebo.

6.2 Postmarketing Experience

The following adverse reactions have been identified during post-approval use of celecoxib. Because these reactions are reported voluntarily from a population of uncertain size, it is not always possible to reliably estimate their frequency or establish a causal relationship to drug exposure.

Cardiovascular:Vasculitis, deep venous thrombosis

General:Anaphylactic reaction, angioedema

Liver and biliary:Liver necrosis, hepatitis, jaundice, hepatic failure

Hemic and lymphatic:Agranulocytosis, aplastic anemia, pancytopenia, leucopenia

Metabolic:Hypoglycemia, hyponatremia

Nervous:Aseptic meningitis, ageusia, anosmia, fatal intracranial hemorrhage

Renal:Interstitial nephritis

Skin and Appendages: Erythema multiforme, exfoliative dermatitis, Stevens-Johnson Syndrome (SJS), toxic epidermal necrolysis (TEN), drug reaction with eosinophilia and systemic symptoms (DRESS), acute generalized exanthematous pustulosis (AGEP), and fixed drug eruption (FDE) [see Warnings and Precautions (5.9)].

7 DRUG INTERACTIONS

See Table 1for clinically significant drug interactions with celecoxib.

Table 1: Clinically Significant Drug Interactions with Celecoxib
Drugs That Interfere with Hemostasis
Clinical Impact | - Celecoxib and anticoagulants such as warfarin have a synergistic effect on bleeding. The concomitant use of celecoxib and anticoagulants have an increased risk of serious bleeding compared to the use of either drug alone. - Serotonin release by platelets plays an important role in hemostasis. Case-control and cohort epidemiological studies showed that concomitant use of drugs that interfere with serotonin reuptake and an NSAID may potentiate the risk of bleeding more than an NSAID alone.
Intervention | Monitor patients with concomitant use of ELYXYB with anticoagulants (e.g., warfarin), antiplatelet drugs (e.g., aspirin), SSRIs, and SNRIs for signs of bleeding [see Warnings and Precautions (5.13)].
Aspirin
Clinical Impact | - In a clinical study, the concomitant use of an NSAID and aspirin was associated with a significantly increased incidence of GI adverse reactions as compared to use of the NSAID alone [see Warnings and Precautions (5.2)]. - In two studies in healthy volunteers and in patients with established heart disease respectively, celecoxib (200 mg to 400 mg daily) has demonstrated a lack of interference with the cardioprotective antiplatelet effect of aspirin (100 mg to 325mg).
Intervention | Concomitant use of ELYXYB and analgesic doses of aspirin is not generally recommended because of the increased risk of bleeding [see Warnings and Precautions (5.13)]. ELYXYB is not a substitute for low dose aspirin for cardiovascular protection.
ACE Inhibitors, Angiotensin Receptor Blockers, and Beta-Blockers
Clinical Impact | - NSAIDs may diminish the antihypertensive effect of ACE inhibiters, ARBs, or beta-blockers (including propranolol). - In patients who are elderly, volume-depleted (including those on diuretic therapy), or have renal impairment, co-administration of an NSAID with ACE inhibitors or ARBs may result in deterioration of renal function, including possible acute renal failure. These effects are usually reversible.
Intervention | - During concomitant use of ELYXYB and ACE inhibitors, ARBs, or beta- blockers, monitor blood pressure to ensure that the desired blood pressure is obtained. - During concomitant use of ELYXYB and ACE inhibitors or ARBs in patients who are elderly, volume-depleted, or have impaired renal function, monitor for signs of worsening renal function [see Warnings and Precautions (5.6)]. - When these drugs are administered concomitantly, patients should be adequately hydrated. Assess renal function at the beginning of the concomitant treatment and periodically thereafter.
Diuretics
Clinical Impact | Clinical studies, as well as postmarketing observations, showed that NSAIDs reduced the natriuretic effect of loop diuretics (e.g., furosemide) and thiazide diuretics in some patients. This effect has been attributed to the NSAID inhibition of renal prostaglandin synthesis.
Intervention | During concomitant use of ELYXYB with diuretics, observe patients for signs of worsening renal function, in addition to assuring diuretic efficacy including antihypertensive effects [see Warnings and Precautions (5.6)].
Digoxin
Clinical Impact | The concomitant use of celecoxib with digoxin has been reported to increase the serum concentration and prolong the half-life of digoxin.
Intervention | During concomitant use of ELYXYB and digoxin, monitor serum digoxin levels.
Lithium
Clinical Impact | NSAIDs have produced elevations in plasma lithium levels and reductions in renal lithium clearance. The mean minimum lithium concentration increased 15%, and the renal clearance decreased by approximately 20%. This effect has been attributed to NSAID inhibition of renal prostaglandin synthesis.
Intervention | During concomitant use of ELYXYB and lithium, monitor patients for signs of lithium toxicity.
Methotrexate
Clinical Impact | Concomitant use of NSAIDs and methotrexate may increase the risk for methotrexate toxicity (e.g., neutropenia, thrombocytopenia, renal dysfunction). Celecoxib has no effect on methotrexate pharmacokinetics.
Intervention | During concomitant use of ELYXYB and methotrexate, monitor patients for methotrexate toxicity.
Cyclosporine
Clinical Impact | Concomitant use of celecoxib and cyclosporine may increase cyclosporine's nephrotoxicity.
Intervention | During concomitant use of ELYXYB and cyclosporine, monitor patients for signs of worsening renal function.
NSAIDs and Salicylates
Clinical Impact | Concomitant use of celecoxib with other NSAIDs or salicylates (e.g., diflunisal, salsalate) increases the risk of GI toxicity [see Warnings and Precautions (5.2)].
Intervention | The concomitant use of ELYXYB with other NSAIDs or salicylates is not recommended.
Pemetrexed
Clinical Impact | Concomitant use of celecoxib and pemetrexed may increase the risk of pemetrexed-associated myelosuppression, renal, and GI toxicity (see the pemetrexed prescribing information).
Intervention | - During concomitant use of ELYXYB and pemetrexed, in patients with renal impairment whose creatinine clearance ranges from 45 to 79 mL/min, monitor for myelosuppression, renal, and GI toxicity. - NSAIDs with short elimination half-lives (e.g., diclofenac, indomethacin) should be avoided for a period of two days before, the day of, and two days following administration of pemetrexed. - In the absence of data regarding potential interaction between pemetrexed and NSAIDs with longer half-lives (e.g., meloxicam, nabumetone), patients taking these NSAIDs should interrupt dosing for at least five days before, the day of, and two days following pemetrexed administration.
CYP2C9 Inhibitors or inducers
Clinical Impact | Celecoxib metabolism is predominantly mediated via cytochrome P450 (CYP) 2C9 in the liver. Co-administration of ELYXYB with drugs that are known to inhibit CYP2C9 (e.g., fluconazole) may enhance the exposure and toxicity of celecoxib whereas co-administration with CYP2C9 inducers (e.g., rifampin) may lead to compromised efficacy of ELYXYB.
Intervention | Evaluate each patient's medical history when consideration is given to prescribing ELYXYB. A dosage adjustment may be warranted when ELYXYB is administered with CYP2C9 inhibitors or inducers.
CYP2D6 substrates
Clinical Impact | In vitrostudies indicate that celecoxib, although not a substrate, is an inhibitor of CYP2D6. Therefore, there is a potential for an in vivodrug interaction with drugs that are metabolized by CYP2D6 (e.g., atomoxetine), and celecoxib may enhance the exposure and toxicity of these drugs.
Intervention | Evaluate each patient's medical history when consideration is given to prescribing ELYXYB. A dosage adjustment may be warranted when ELYXYB is administered with CYP2D6 substrates.
Corticosteroids
Clinical Impact | Concomitant use of corticosteroids with celecoxib may increase the risk of GI ulceration or bleeding.
Intervention | Monitor patients with concomitant use of ELYXYB with corticosteroids for signs of bleeding [see Warnings and Precautions (5.2)].

8 USE IN SPECIFIC POPULATIONS

8.1 Pregnancy

Risk Summary

Use of NSAIDs, including ELYXYB, can cause premature closure of the fetal ductus arteriosus and fetal renal dysfunction leading to oligohydramnios and, in some cases, neonatal renal impairment. Because of these risks, limit dose and duration of ELYXYB use between about 20 and 30 weeks of gestation, and avoid ELYXYB use at about 30 weeks of gestation and later in pregnancy (see Clinical Considerations, Data).

Premature Closure of Fetal Ductus Arteriosus

Use of NSAIDs, including ELYXYB, at about 30 weeks gestation or later in pregnancy increases the risk of premature closure of the fetal ductus arteriosus.

Oligohydramnios/Neonatal Renal Impairment

Use of NSAIDs at about 20 weeks gestation or later in pregnancy has been associated with cases of fetal renal dysfunction leading to oligohydramnios, and in some cases, neonatal renal impairment.

Data from observational studies regarding other potential embryofetal risks of NSAID use in women in the first or second trimesters of pregnancy are inconclusive. In animal reproduction studies, administration of celecoxib during pregnancy resulted in adverse effects on development, including increases in embryonic death and fetal malformations, at doses or maternal plasma drug exposures greater than those used clinically (see Data). Based on animal data, prostaglandins have been shown to have an important role in endometrial vascular permeability, blastocyst implantation, and decidualization. In animal studies, administration of prostaglandin synthesis inhibitors such as celecoxib, resulted in increased pre- and post- implantation loss. Prostaglandins also have been shown to have an important role in fetal kidney development. In published animal studies, prostaglandin synthesis inhibitors have been reported to impair kidney development when administered at clinically relevant doses.

All pregnancies have a background risk of birth defects, loss, or other adverse outcomes. In the U.S. general population, the estimated background risk of major birth defects and miscarriage in clinically recognized pregnancies is 2-4% and 15-20%, respectively. The reported rate of major birth defects among deliveries to women with migraine ranged from 2.2% to 2.9% and the reported rate of miscarriage was 17%, which were similar to rates reported in women without migraine.

Clinical Considerations

Fetal/Neonatal Adverse Reactions

Premature Closure of Fetal Ductus Arteriosus:

Avoid use of NSAIDs in women at about 30 weeks gestation and later in pregnancy, because NSAIDs, including ELYXYB, can cause premature closure of the fetal ductus arteriosus (see Data).

Oligohydramnios/Neonatal Renal Impairment

If an NSAID is necessary at about 20 weeks gestation or later in pregnancy, limit the use to the lowest effective dose and shortest duration possible. If ELYXYB treatment extends beyond 48 hours, consider monitoring with ultrasound for oligohydramnios. If oligohydramnios occurs, discontinue ELYXYB and follow up according to clinical practice (see Data).

Labor or Delivery

There are no studies on the effects of celecoxib during labor or delivery. In animal studies, NSAIDs, including celecoxib, inhibit prostaglandin synthesis, cause delayed parturition, and increase the incidence of stillbirth.

Data

Human Data

Premature Closure of Fetal Ductus Arteriosus:

Published literature reports that the use of NSAIDs at about 30 weeks of gestation and later in pregnancy may cause premature closure of the fetal ductus arteriosus.

Oligohydramnios/Neonatal Renal Impairment:

Published studies and postmarketing reports describe maternal NSAID use at about 20 weeks gestation or later in pregnancy associated with fetal renal dysfunction leading to oligohydramnios, and in some cases, neonatal renal impairment. These adverse outcomes are seen, on average, after days to weeks of treatment, although oligohydramnios has been infrequently reported as soon as 48 hours after NSAID initiation. In many cases, but not all, the decrease in amniotic fluid was transient and reversible with cessation of the drug. There have been a limited number of case reports of maternal NSAID use and neonatal renal dysfunction without oligohydramnios, some of which were irreversible. Some cases of neonatal renal dysfunction required treatment with invasive procedures, such as exchange transfusion or dialysis.

Methodological limitations of these postmarketing studies and reports include lack of a control group; limited information regarding dose, duration, and timing of drug exposure; and concomitant use of other medications. These limitations preclude establishing a reliable estimate of the risk of adverse fetal and neonatal outcomes with maternal NSAID use. Because the published safety data on neonatal outcomes involved mostly preterm infants, the generalizability of certain reported risks to the full-term infant exposed to NSAIDs through maternal use is uncertain.

Animal data

Administration of celecoxib to rats during early embryonic development resulted in increased pre- and postimplantation loss at oral doses ≥50 mg/kg/day, which was associated with plasma exposure (AUC) approximately 20 times that in humans at the maximum recommended dose (MRHD) of 120 mg/day.

Administration of celecoxib to pregnant rats throughout the period of organogenesis resulted in increased incidences of a specific fetal malformation (diaphragmatic hernia) at oral doses ≥30 mg/kg/day, associated with plasma exposure (AUC) approximately 20 times that in humans at the MRHD.

Administration of celecoxib to pregnant rabbits throughout organogenesis produced increased incidences of fetal visceral (ventricular septal defects) and skeletal malformations at oral doses

≥150 mg/kg/day, associated with maternal plasma AUC approximately 7 times that in humans at the MRHD.

Celecoxib produced no evidence of delayed labor or parturition in rats at oral doses up to 100 mg/kg/day, which was associated with maternal plasma AUC approximately 25 times that in humans at the MRHD.

8.2 Lactation

Risk Summary

Limited data from 3 published reports that included a total of 12 breastfeeding women showed low levels of celecoxib in breast milk. The calculated average daily infant dose was 10 to 40 mcg/kg/day, less than 1% of the weight-based therapeutic dose for a two-year old-child. A report of two breastfed infants who were 17 and 22 months of age did not show any adverse events. There is no information available regarding the effects of celecoxib on milk production. The developmental and health benefits of breastfeeding should be considered along with the mother's clinical need for ELYXYB and any potential adverse effects on the breastfed infant from the celecoxib or from the underlying maternal condition.

8.3 Females and Males of Reproductive Potential

Infertility

Females

Based on the mechanism of action, the use of prostaglandin-mediated NSAIDs, including ELYXYB, may delay or prevent rupture of ovarian follicles, which has been associated with reversible infertility in some women. Published animal studies have shown that administration of prostaglandin synthesis inhibitors has the potential to disrupt prostaglandin mediated follicular rupture required for ovulation. Small studies in women treated with NSAIDs have also shown a reversible delay in ovulation. Consider withdrawal of NSAIDs, including ELYXYB, in women who have difficulties conceiving or who are undergoing investigation of infertility.

8.4 Pediatric Use

Safety and effectiveness in pediatric patients have not been established. Disseminated intravascular coagulation has occurred in pediatric patients [see Warnings and Precautions (5.16)].

8.5 Geriatric Use

Elderly patients, compared to younger patients, are at greater risk for NSAID-associated serious cardiovascular, gastrointestinal, and/or renal adverse reactions. If the anticipated benefit for the elderly patient outweighs these potential risks, treat for the fewest number of days per month, as needed, and monitor patients for adverse effects [see Warnings and Precautions (5.1, 5.2, 5.3, 5.6, 5.15)].

In the controlled clinical trials for migraine, approximately 70 patients were ≥ 65 years of age. Of the total number of patients who received celecoxib (for indications other than migraine) in pre-approval clinical trials, more than 3,300 were 65-74 years of age, while approximately 1,300 additional patients were 75 years and over. No substantial differences in effectiveness were observed between these subjects and younger subjects. In clinical studies comparing renal function as measured by the GFR, BUN and creatinine, and platelet function as measured by bleeding time and platelet aggregation, the results were not different between elderly and young volunteers.

However, as with other NSAIDs, including those that selectively inhibit COX-2, there have been more spontaneous postmarketing reports of fatal GI events and acute renal failure in the elderly than in younger patients [see Warnings and Precautions (5.4, 5.6)].

8.6 Hepatic Impairment

No dosage adjustment is needed for patients with mild hepatic impairment (Child-Pugh Class A). Reduce the dose of ELYXYB in patients with moderate hepatic impairment (Child-Pugh Class B) [see Dosage and Administration (2.2) and Clinical Pharmacology (12.3)]. The use of ELYXYB in patients with severe hepatic impairment (Child-Pugh Class C) is not recommended.

8.7 Renal Impairment

No dosage adjustment is needed for patients with mild or moderate renal impairment. ELYXYB is not recommended in patients with severe renal impairment [see Warnings and Precautions (5.6) and Clinical Pharmacology (12.3)].

8.8 Poor Metabolizers of CYP2C9 Substrates

In patients who are known or suspected to be poor CYP2C9 metabolizers (i.e., CYP2C9*3/*3), based on genotype or previous history/experience with other CYP2C9 substrates (e.g., warfarin, phenytoin) reduce the dose of ELYXYB [see Dosage and Administration (2.3) and Clinical Pharmacology (12.5)].

10 OVERDOSAGE

Symptoms following acute NSAID overdosages have been typically limited to lethargy, drowsiness, nausea, vomiting, and epigastric pain, which have been generally reversible with supportive care. Gastrointestinal bleeding has occurred. Hypertension, acute renal failure, respiratory depression, and coma have occurred, but were rare [see Warnings and Precautions (5.1, 5.2, 5.4, 5.6)].

No overdoses of celecoxib were reported during clinical trials. No information is available regarding the removal of celecoxib by hemodialysis, but based on its high degree of plasma protein binding (>97%), dialysis is unlikely to be useful in overdose.

Manage patients with symptomatic and supportive care following an NSAID overdosage. There are no specific antidotes. Consider emesis and/or activated charcoal (60 to 100 grams in adults, 1 to 2 grams per kg of body weight in pediatric patients) and/or osmotic cathartic in symptomatic patients seen within four hours of ingestion or in patients with a large overdosage (5 to 10 times the recommended dosage). Forced diuresis, alkalinization of urine, hemodialysis, or hemoperfusion may not be useful due to high protein binding.

For additional information about overdosage treatment contact a poison control center.

11 DESCRIPTION

ELYXYB is an oral solution of celecoxib, a nonsteroidal anti-inflammatory drug. Each unit dose of ELYXYB contains 120 mg of celecoxib. Celecoxib is a white or almost white, crystalline or amorphous powder with a pKa of 11. Celecoxib is hydrophobic (log P is 3.0) and practically insoluble in water. Celecoxib is chemically designated as p-[5- p-tolyl-3-(trifluoromethyl) pyrazol-1-yl] benzenesulfonamide. The empirical formula for celecoxib is C17H14F3N3O2S, and the molecular weight is 381.37. It has the following chemical structure:

The inactive ingredients in ELYXYB include: acesulfame potassium, banana flavor, bubble gum flavor, ethyl alcohol, glycerin, glyceryl monocaprylate, L-menthol, lauroyl polyoxyl-32 glycerides, medium chain triglycerides, monoammonium glycyrrhizinate, peppermint flavor, polyoxyl 35 castor oil, polyoxyl 40 hydrogenated castor oil, propyl gallate, purified water, and sucralose.

12 CLINICAL PHARMACOLOGY

12.1 Mechanism of Action

Celecoxib is a nonsteroidal anti-inflammatory drug with analgesic, anti-inflammatory, and antipyretic properties.

The mechanism of action by which celecoxib exerts therapeutic effects in migraine patients is not fully understood but may involve inhibition of prostaglandin synthesis, primarily via inhibition of COX-2.

12.2 Pharmacodynamics

Platelets

In clinical trials using normal volunteers, celecoxib at single doses up to 800 mg and multiple doses of 600 mg twice daily for up to 7 days duration (higher than recommended therapeutic doses) had no effect on reduction of platelet aggregation or increase in bleeding time.

Because of its lack of platelet effects, celecoxib is not a substitute for aspirin for cardiovascular prophylaxis. It is not known if there are any effects of celecoxib on platelets that may contribute to the increased risk of serious cardiovascular thrombotic adverse events associated with the use of celecoxib.

Fluid Retention

Inhibition of PGE2 synthesis may lead to sodium and water retention through increased reabsorption in the renal medullary thick ascending loop of Henle and perhaps other segments of the distal nephron. In the collecting ducts, PGE2 appears to inhibit water reabsorption by counteracting the action of antidiuretic hormone.

12.3 Pharmacokinetics

Celecoxib exhibits a dose-proportional increase in exposure after once daily oral administration of 120 to 240 mg doses (2 times the recommended dosage) of ELYXYB.

Absorption

Following administration of 120 mg of ELYXYB under fasting condition in 24 healthy subjects, the median time to peak plasma levels (i.e., Tmax) of celecoxib was 1 hour (range 0.67 to 3.00).

Food Effect

When ELYXYB was taken with a high-fat meal, the median time to peak plasma levels (i.e., Tmax) was delayed by 2 hours with an approximately 50% decrease in Cmaxand no change in total absorption (i.e., AUC) compared to fasting conditions. However, in Study 1 and Study 2, ELYXYB was administered without regard to food [see Dosage and Administration (2.1), Clinical Studies (14)].

Distribution

In healthy subjects, celecoxib is highly protein bound (~97%) within the clinical dose range. In vitro studies indicate that celecoxib binds primarily to albumin and, to a lesser extent, α1-acid glycoprotein. The apparent volume of distribution following single dose administration of ELYXYB at fasting state is (Vz/F) is approximately 288 L, suggesting extensive distribution into the tissues. Celecoxib is not preferentially bound to red blood cells.

Elimination

Metabolism

Celecoxib metabolism is primarily mediated via CYP2C9. Three metabolites, a primary alcohol, the corresponding carboxylic acid, and its glucuronide conjugate, have been identified in human plasma. These metabolites are inactive as COX-1 or COX-2 inhibitors.

Excretion

Celecoxib is eliminated predominantly by hepatic metabolism with little (<3%) unchanged drug recovered in the urine and feces. Following a single oral dose of radiolabeled drug, approximately 57% of the dose was excreted in the feces and 27% was excreted into the urine. The primary metabolite in both urine and feces was the carboxylic acid metabolite (73% of dose) with low amounts of the glucuronide also appearing in the urine. The mean apparent elimination t½ of celecoxib from ELYXYB was approximately 6 hours independent of dosing condition and similar to that observed for Celebrex under fed conditions.

Specific Populations

Geriatric

At steady state, elderly subjects (over 65 years old) had a 40% higher Cmaxand a 50% higher AUC compared to the younger subjects for celecoxib oral capsules. In elderly females, celecoxib Cmaxand AUC are higher than those for elderly males, but these increases are predominantly due to lower body weight in elderly females. Dose adjustment in the elderly is not generally necessary.

Race

Meta-analysis of pharmacokinetic studies conducted using celecoxib oral capsules has suggested an approximately 40% higher AUC of celecoxib in Blacks compared to Caucasians. The cause and clinical significance of this finding is unknown.

Hepatic Impairment

The effect of hepatic impairment on the pharmacokinetics of ELYXYB has not been evaluated. A pharmacokinetic study in subjects with mild (Child-Pugh Class A) and moderate (Child-Pugh Class B) hepatic impairment conducted using celecoxib oral capsule has shown that steady-state celecoxib AUC is increased about 40% and 180%, respectively, above that seen in healthy control subjects [see Dosage and Administration (2.2) and Use in Specific Populations (8.6)]. Patients with severe hepatic impairment (Child-Pugh Class C) have not been studied.

Renal Impairment

In a cross-study comparison done for celecoxib oral capsules, celecoxib AUC was approximately 40% lower in patients with chronic renal impairment (GFR 35-60 mL/min) than that seen in subjects with normal renal function. No significant relationship was found between GFR and celecoxib clearance. Patients with severe renal impairment have not been studied [see Warnings and Precautions (5.6) and Use in Specific Populations (8.6)].

Drug Interaction Studies

In vitro studies indicate that celecoxib is not an inhibitor of cytochrome P450 2C9, 2C19, or 3A4. In vivo studies have shown the following:

Aspirin

When NSAIDs were administered with aspirin, the protein binding of NSAIDs was reduced, although the clearance of free NSAID was not altered. The clinical significance of this interaction is not known [see Drug Interactions (7)].

Lithium

In a study conducted in healthy subjects, mean steady-state lithium plasma levels increased approximately 17% in subjects receiving lithium 450 mg twice daily with celecoxib 200 mg oral capsule twice daily as compared to subjects receiving lithium alone [see Drug Interactions (7)].

Fluconazole

Concomitant administration of fluconazole at 200 mg once daily resulted in a two-fold increase in celecoxib plasma concentration. This increase is due to the inhibition of celecoxib metabolism via P450 2C9 by fluconazole [see Drug Interactions (7) ].

Other Drugs

The effects of celecoxib on the pharmacokinetics and/or pharmacodynamics of glyburide, ketoconazole, phenytoin, and tolbutamide have been studied in vivousing celecoxib oral capsules and clinically important interactions have not been found.

12.5 Pharmacogenomics

CYP2C9 activity is reduced in individuals with genetic polymorphisms that lead to reduced enzyme activity, such as those homozygous for the CYP2C9*2 and CYP2C9*3 polymorphisms. Limited data from 4 published reports that included a total of 8 subjects with the homozygous CYP2C9*3/*3 genotype showed celecoxib systemic levels that were 3- to 7-fold higher in these subjects compared to subjects with CYP2C9*1/*1 or *I/*3 genotypes. The pharmacokinetics of celecoxib have not been evaluated in subjects with other CYP2C9 polymorphisms, such as *2, *5, *6, *9, and *11. It is estimated that the frequency of the homozygous *3/*3 genotype is 0.3% to 1.0% in various ethnic groups [see Dosage and Administration (2.3) and Use in Specific Populations (8.8)].

13 NONCLINICAL TOXICOLOGY

13.1 Carcinogenesis, Mutagenesis, Impairment of Fertility

Carcinogenesis

Celecoxib was not carcinogenic when administered orally for two years to rats at oral doses up to 200 mg/kg for males and 10 mg/kg for females (associated with plasma exposures (AUC) approximately 14 and 7 times, respectively, that in humans at the maximum recommended human dose (MRHD) of 120 mg/day) or in mice at oral doses up to 25 mg/kg for males and 50 mg/kg for females (associated with plasma AUCs approximately 4 times in humans at the MRHD).

Mutagenesis

Celecoxib was not mutagenic in an Ames test and a mutation assay in Chinese hamster ovary (CHO) cells, nor clastogenic in a chromosome aberration assay in CHO cells and an in vivomicronucleus test in rat bone marrow.

Impairment of Fertility

Administration of celecoxib to male and female rats prior to and during mating and continuing in females through implantation had no effect on fertility or male reproductive function at oral doses up to 600 mg/kg/day, which were associated with plasma AUCs approximately 40 times that in humans at the MRHD. Increased implantation loss was observed at doses ≥50 mg/kg/day, which was associated with plasma AUC approximately 20 times that in humans at the MRHD.

13.2 Animal Toxicology and/or Pharmacology

An increase in the incidence of background findings of spermatocele with or without secondary changes such as epididymal hypospermia as well as minimal to slight dilation of the seminiferous tubules were seen in the juvenile rat. These reproductive findings while apparently treatment-related did not increase in incidence or severity with dose and may indicate an exacerbation of a spontaneous condition. Similar reproductive findings were not observed in studies of juvenile or adult dogs or in adult rats treated with celecoxib. The clinical significance of this observation is unknown.

14 CLINICAL STUDIES

14.1 Migraine

The efficacy of ELYXYB for the acute treatment of migraine with or without aura was demonstrated in two randomized, double-blind, placebo-controlled clinical trials [Study 1 (NCT03009019) and Study 2 (NCT03006276)]. In Study 1, patients were randomized to receive ELYXYB 120 mg (n=316) or placebo (n=315); in Study 2, patients were also randomized to receive ELYXYB 120 mg (n=311) or placebo (n=311). In both studies, patients were instructed to treat a migraine with moderate to severe pain intensity.

Patients enrolled in the trials were predominantly female (86%) and White (74%), with a mean age of 40.6 years (range 18 to 75 years).

The primary efficacy analyses were conducted in patients who treated a migraine with moderate to severe pain. The efficacy of ELYXYB was established by an effect on pain freedom at 2 hours post-dose and most bothersome symptom (MBS) freedom at 2 hours post-dose. Pain freedom was defined as a reduction of moderate or severe headache pain to no pain, and MBS freedom was defined as the absence of the self-identified MBS (photophobia, phonophobia, or nausea). Among patients who selected a MBS, the most commonly selected MBS was photophobia (56%), followed by nausea (25%), and phonophobia (18%).

In both studies, the percentage of patients achieving MBS freedom at 2 hours post-dose was significantly greater among patients receiving ELYXYB, compared to those receiving placebo. In Study 2, the percentage of patients achieving headache pain freedom at 2 hours post-dose was significantly greater among patients receiving ELYXYB, compared to those receiving placebo (see Table 2).

Table 2: Migraine Efficacy Endpoints for Study 1 and Study 2
 | Study 1 |  | Study 2
 | Placebo | ELYXYB 120 mg | Placebo | ELYXYB 120 mg
Pain Free at 2 hours
N | 273 | 284 | 271 | 279
% Responders | 25.3 | 32.4 | 21.0 | 35.1
Difference from placebo (%) |  | 7 |  | 14
p-value |  | 0.076a |  | <0.001
Most Bothersome Symptom Free at 2 hours
N | 234 | 245 | 237 | 236
% Responders | 44.4 | 58.0 | 43.9 | 56.8
Difference from placebo (%) |  | 14 |  | 13
p-value |  | 0.003 |  | 0.006
aNot statistically significant

16 HOW SUPPLIED/STORAGE AND HANDLING

16.1 How Supplied

ELYXYB (celecoxib) oral solution, 120 mg/4.8 mL (25 mg/mL) is a clear colorless oral solution supplied in a disposable glass bottle with a child resistant cap.

Each carton (NDC 69557-333-01) contains six (6) glass bottles, a Full Prescribing Information, Medication Guide, and Instructions for Use.

16.2 Storage and Handling

Store at room temperature 20°C to 25°C (68°F to 77°F); excursions permitted between 15°C to 30°C (59°F to 86°F) [see USP Controlled Room Temperature].

Do not refrigerate or freeze.

Unused portion should be discarded immediately after use.

17 PATIENT COUNSELING INFORMATION

Advise the patient to read the FDA-approved patient labeling (Medication Guide and Instructions for Use).

Administration Information

For patients who are prescribed the recommended dosage of 120 mg, instruct them to drink the entire amount of ELYXYB directly from the bottle.

For patients who are prescribed the reduced dosage (i.e., patients with moderate hepatic impairment or CYP2C9 poor metabolizers), instruct them to use an oral dosing syringe to correctly measure the prescribed amount of medication. Inform these patients that oral dosing syringes may be obtained from their pharmacy and that a household teaspoon is not an accurate measuring device. Instruct these patients to discard the unused portion of ELYXYB.

Cardiovascular Thrombotic Events

Advise patients to be alert for the symptoms of cardiovascular thrombotic events, including chest pain, shortness of breath, weakness, or slurring of speech, and to report any of these symptoms to their health care provider immediately [see Warnings and Precautions (5.1)].

Gastrointestinal Bleeding, Ulceration, and Perforation

Advise patients to report symptoms of ulcerations and bleeding, including epigastric pain, dyspepsia, melena, and hematemesis to their health care provider. In the setting of concomitant use of low-dose aspirin for cardiac prophylaxis, inform patients of the increased risk for and the signs and symptoms of GI bleeding [see Warnings and Precautions (5.2)].

Hepatotoxicity

Inform patients of the warning signs and symptoms of hepatotoxicity (e.g., nausea, fatigue, lethargy, pruritus, diarrhea jaundice, right upper quadrant tenderness, and “flu-like” symptoms). If these occur, instruct patients to stop ELYXYB and seek immediate medical therapy [see Warnings and Precautions (5.3) and Use in Specific Populations (8.6)].

Heart Failure and Edema

Advise patients to be alert for the symptoms of congestive heart failure including shortness of breath, unexplained weight gain, or edema and to contact their healthcare provider if such symptoms occur [see Warnings and Precautions (5.5)].

Anaphylactic Reactions

Inform patients of the signs of an anaphylactic reaction (e.g., difficulty breathing, swelling of the face or throat). Instruct patients to seek immediate emergency help if these occur [see Contraindications (4) and Warnings and Precautions (5.7)].

Serious Skin Reactions, including DRESS

Advise patients to stop taking ELYXYB immediately if they develop any type of rash or fever and to contact their healthcare provider as soon as possible [see Warnings and Precautions (5.9, 5.10)].

Medication Overuse Headache

Inform patients that use of acute migraine drugs for 10 or more days per month, including ELYXYB, may lead to an exacerbation of headache and encourage patients to record headache frequency and drug use (e.g., by keeping a headache diary). Instruct patients to contact their healthcare provider if the frequency of their migraines increases; withdrawal of ELYXYB may be necessary [see Warnings and Precautions (5.11)].

Female Fertility

Advise females of reproductive potential who desire pregnancy that NSAIDs, including ELYXYB, may be associated with a reversible delay in ovulation [see Use in Specific Populations (8.3)].

Fetal Toxicity

Inform pregnant women to avoid use of ELYXYB and other NSAIDs starting at 30 weeks gestation because of the risk of the premature closing of the fetal ductus arteriosus. If treatment with ELYXYB is needed for a pregnant woman between about 20 to 30 weeks gestation, advise her that she may need to be monitored for oligohydramnios, if treatment continues for longer than 48 hours [see Warnings and Precautions (5.12) and Use in Specific Populations (8.1)] .

Avoid Concomitant Use of NSAIDs

Inform patients that the concomitant use of ELYXYB with other NSAIDs or salicylates (e.g., diflunisal, salsalate) is not recommended due to the increased risk of gastrointestinal toxicity, and little or no increase in efficacy [see Warnings and Precautions (5.2) and Drug Interactions (7)]. Alert patients that NSAIDs may be present in “over the counter” medications for treatment of colds, fever, or insomnia.

Use of NSAIDs and Low-Dose Aspirin

Inform patients not to use low-dose aspirin concomitantly with ELYXYB until they talk to their healthcare provider [see Drug Interactions (7)].

ELYXYB is a trademark of SCILEX Pharmaceuticals Inc.

Manufactured by: Contract Pharmaceuticals Limited, Mississauga, Ontario, Canada

Manufactured for: SCILEX Pharmaceuticals Inc., Palo Alto, CA 94303

Active Ingredient Made in India

©2023 SCILEX Pharmaceuticals Inc. All rights reserved.

ELY-00194 11/2024

Medication Guide
ELYXYB (ee-lix'-ib)) (celecoxib) oral solution

What is the most important information I should know about ELYXYB?
ELYXYB contains celecoxib (a non-steroidal anti-inflammatory drug or NSAID). NSAIDs, including ELYXYB, can cause serious side effects, including:

- Increased risk of a heart attack or stroke that can lead to death.This risk may happen early in treatment and may increase:
  - with increasing doses of NSAIDs
  - with longer use of NSAIDs

Do not take ELYXYB right before or after a heart surgery called a “coronary artery bypass graft (CABG)."
Avoid taking NSAIDs, including ELYXYB, after a recent heart attack, unless your healthcare provider tells you to. You may have an increased risk of another heart attack if you take NSAIDs after a recent heart attack.

- Increased risk of bleeding, ulcers, and tears (perforation) of the esophagus (tube leading from the mouth to the stomach), stomach and intestines:
  - anytime during use
  - without warning symptoms
  - that may cause death

The risk of getting an ulcer or bleeding increases with:

- past history of stomach ulcers, or stomach or intestinal bleeding with use of NSAIDs
- taking medicines called “corticosteroids”, “antiplatelet drugs”, “anticoagulants”, “SSRIs” or “SNRIs”

- increasing doses of NSAIDs
- longer use of NSAIDs
- smoking
- drinking alcohol

- older age
- poor health
- advanced liver disease
- bleeding problems

ELYXYB should only be used:

- exactly as prescribed
- for the shortest time needed

What is ELYXYB?
ELYXYB is a prescription medicine used for the acute treatment of migraine attacks with or without aura in adults.

- ELYXYB is not used as a preventive treatment of migraine.
- It is not known if ELYXYB is safe and effective in children.

Who should not take ELYXYB? Do not take ELYXYB:

- if you are allergic to celecoxib or any of the ingredients in ELYXYB. See the end of this Medication Guide for a complete list of ingredients in ELYXYB.
- If you are allergic to sulfonamides.
- if you have had an asthma attack, hives, or other allergic reaction with aspirin or any other NSAIDs.
- right before or after heart bypass surgery.

Before taking ELYXYB, tell your healthcare provider about all of your medical conditions, including if you:

- have liver or kidney problems.
- have a history of stomach ulcer or bleeding in your stomach or intestines.
- have heart disease or risk factors that increase your chance of getting heart disease.
- have high blood pressure.
- have asthma.
- are pregnant or plan to become pregnant. Taking NSAIDs, including ELYXYB, at about 20 weeks of pregnancy or later may harm your unborn baby. If you need to take NSAIDs for more than 2 days when you are between 20 and 30 weeks of pregnancy, your healthcare provider may need to monitor the amount of fluid in your womb around your baby. You should not take NSAIDs after about 30 weeks of pregnancy.
- are breastfeeding or plan to breast feed. ELYXYB may pass into your breast milk. Talk with your healthcare provider about the best way to feed your baby if you take ELYXYB.

Tell your healthcare provider about all of the medicines you take, including prescription or over- the-counter medicines, vitamins or herbal supplements.NSAIDs, including ELYXYB, and some other medicines can interact with each other and cause serious side effects. Do not start taking any new
medicine without talking to your healthcare provider first.

How should I take ELYXYB?
See the detailed “ Instructions for Use” on how to take ELYXYB solution.

- Take ELYXYB exactly as your healthcare provider tells you to take it.
- Take ELYXYB by mouth with or without food.
- Do not take more than one dose in a 24-hour period.
- Use ELYXYB for the fewest number of days a month, as needed.

What are the possible side effects of ELYXYB?
ELYXYB can cause serious side effects, including:
See “ What is the most important information I should know about ELYXYB?

- liver problems including liver failure
- new or worse high blood pressure
- heart failure
- kidney problems including kidney failure
- life-threatening allergic reactions
- asthma attacks in people who have asthma
- life-threatening skin reactions
- medication overuse headaches. Some people who use too much ELYXYB may have worse headaches (medication overuse headache). If your headaches get worse, your healthcare provider may decide to stop your treatment with ELYXYB.
- low red blood cells (anemia)
- Other side effects of NSAIDs include:stomach pain, constipation, diarrhea, gas, heartburn, nausea, vomiting, and dizziness.

Get emergency help right away if you get any of the following symptoms:

- shortness of breath or trouble breathing
- chest pain
- weakness in one part or side of your body

- slurred speech
- swelling of the face or throat

Stop taking ELYXYB and call your healthcare provider right away if you get any of the following symptoms:

- nausea
- more tired or weaker than usual
- diarrhea
- itching
- your skin or eyes look yellow
- indigestion or stomach pain
- flu-like symptoms

- vomit blood
- there is blood in your bowel movement or it is black and sticky like tar
- unusual weight gain
- skin rash or blisters with fever
- swelling of the arms, legs, hands and feet

If you take too much ELYXYB, call your healthcare provider or get medical help right away.
These are not all the possible side effects of NSAIDs. For more information, ask your healthcare provider or pharmacist about NSAIDs. Call your doctor for medical advice about side effects. You may report side effects to FDA at 1-800-FDA-1088.

Other information about NSAIDs

- Aspirin is an NSAID but it does not increase the chance of a heart attack. Aspirin can cause bleeding in the brain, stomach, and intestines. Aspirin can also cause ulcers in the stomach and intestines.
- Some NSAIDs are sold in lower doses without a prescription (over-the counter). Talk to your healthcare provider before using over- the-counter NSAIDs for more than 10 days.

General information about the safe and effective use of ELYXYB

Medicines are sometimes prescribed for purposes other than those listed in a Medication Guide. Do not use ELYXYB for a condition for which it was not prescribed. Do not give ELYXYB to other people, even if they have the same symptoms that you have. It may harm them.
If you would like more information about ELYXYB, talk with your healthcare provider. You can ask your pharmacist or healthcare provider for information about ELYXYB that is written for health professionals.

Manufactured by: Contract Pharmaceuticals Limited, Mississauga, Ontario, Canada Manufactured for: SCILEX Pharmaceuticals Inc., Palo Alto, CA 94303
Active Ingredient Made in India
ELY-00084 06/2023

This Medication Guide has been approved by the U.S. Food and Drug Administration.

Revised: June 2023

Instructions For Use

ELYXYB (ee-lix'-ib) (celecoxib)

oral solution 25 mg/mL

Read this Instructions for Use before you start taking ELYXYB and each time you get a refill. There may be new information. This leaflet does not take the place of talking to your healthcare provider about your medical condition or treatment. Take ELYXYB exactly how your healthcare provider tells you to.

If your healthcare provider has prescribed 120 mg of ELYXYB, take all of the medicine in the bottle as described below in Instructions-1.

If your healthcare provider has prescribed 60 mg of ELYXYB, take 2.4 mL of the medicine, as described in Instructions-2. You will need a dosing syringe from the pharmacy to give the right amount of medicine. Do notuse a household teaspoon to measure ELYXYB.

Instructions-1 (Full dose of 120 mg)

Step 1: When you need to take ELYXYB, push down the cap and turn it to the left (counterclockwise) to open it.

Step 2: When taking 120 mg of ELYXYB, drink it directly from the bottle. Hold the bottle upside down for 10 seconds to make sure the full amount of medicine is taken.

Step 3: Close the bottle by turning the cap to the right (clockwise) right away after drinking the medicine.

Step 4: Throw away (discard) the bottle.

Step 5: After you take ELYXYB, you may drink up to 8 ounces (240 mL) of water.

Instructions-2 (50% reduced dose of 60 mg)

Step 1: When you need to take ELYXYB, push down the cap and turn it to the left (counterclockwise to open it.

Step 2: Use an oral dosing syringe (3 mL or 5 mL) from your pharmacy to withdraw 2.4 mL of ELYXYB. Insert the syringe through ELYXYB bottle opening and draw up 2.4 mL of ELYXYB directly from the bottle into the syringe. This 2.4 mL will be your 60 mg dose.
Note: Do not use a household teaspoon to measure ELYXYB.

Step 3: Place the 2.4 mL of the ELYXYB that is in the dosing syringe in your mouth and swallow it right away.

Step 4: Close the bottle tightly by turning the cap to the right (clockwise) right away after taking the correct dose of ELYXYB.
Note: Do not store the bottle to reuse the remaining medicine.

Step 5: Throw away (discard) the bottle with the unused ELYXYB.

Step 6: After you take ELYXYB, you may drink up to 8 ounces (240 mL) of water.

These Instructions for Use have been approved by the U.S. Food and Drug Administration Revised: June 2023 For more information call SCILEX Pharmaceuticals Inc. at 1-866-SCILEX3.

Manufactured by: Contract Pharmaceuticals Limited, Mississauga, Ontario, Canada Manufactured for: SCILEX Pharmaceuticals Inc., Palo Alto, CA 94303

Active Ingredient Made in India

ELYXYB is a trademark of SCILEX Pharmaceuticals Inc.

©2023 SCILEX Pharmaceuticals Inc. All rights reserved.

ELY-00085 06/2023

SCILEX®
PHARMACEUTICALS

Principal Display Panel – 4.8 mL Carton Label

SCILEX®PHARMACEUTICALS

NDC 69557-333-01

Elyxyb™

(celecoxib)

Oral Solution

120 mg/4.8 mL
(25 mg/mL)

For Oral use only

Rx Only

Discard unused portion immediately after use.

Do not store or reuse leftover Elyxyb oral solution.

Warning: Keep out of reach of children.

Warning: Check the dose your healthcare provider has prescribed.

Pharmacist:

Dispense in this sealed carton, which contains six (6) unit dose glass bottles.

Dispense the enclosed Medication Guide to each patient.